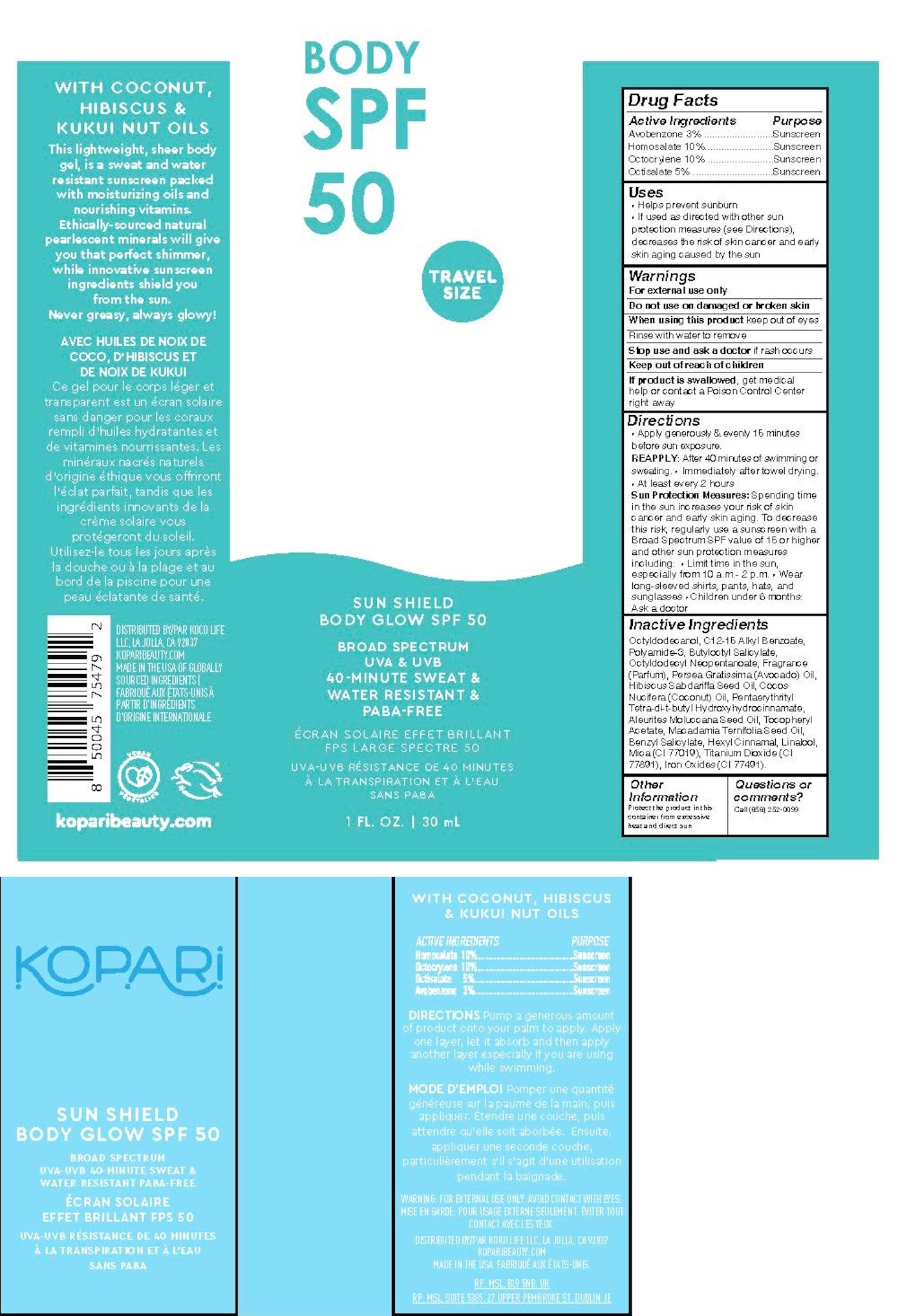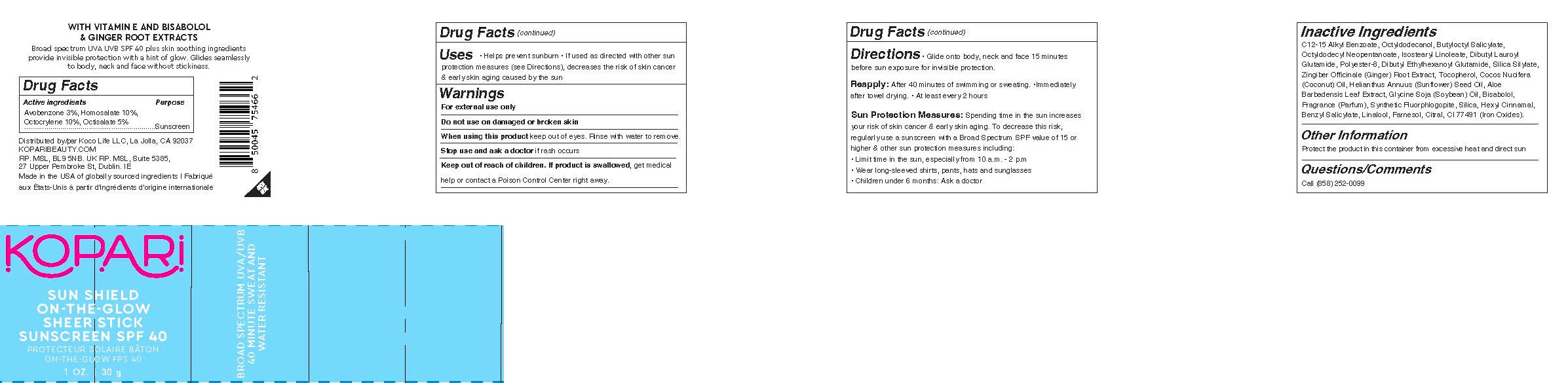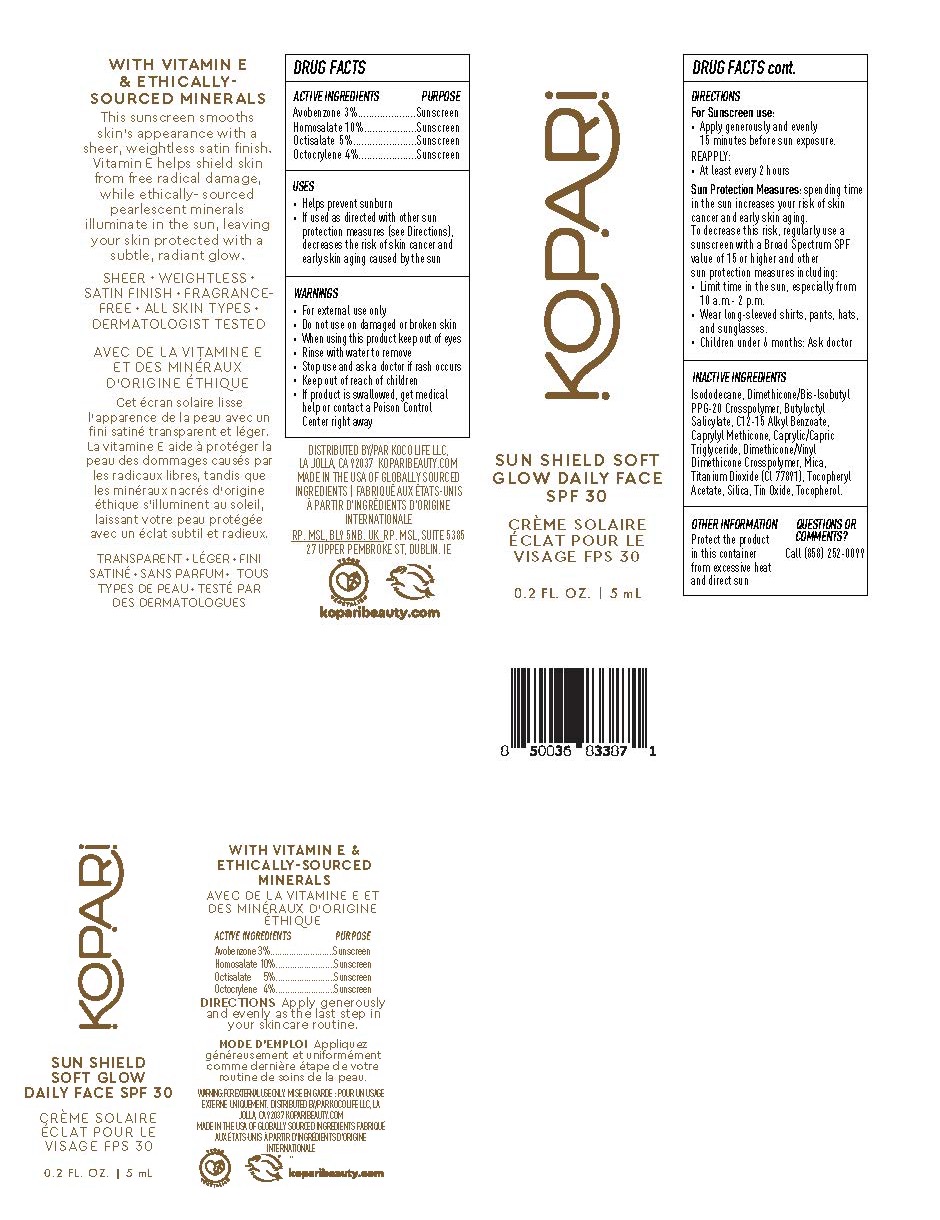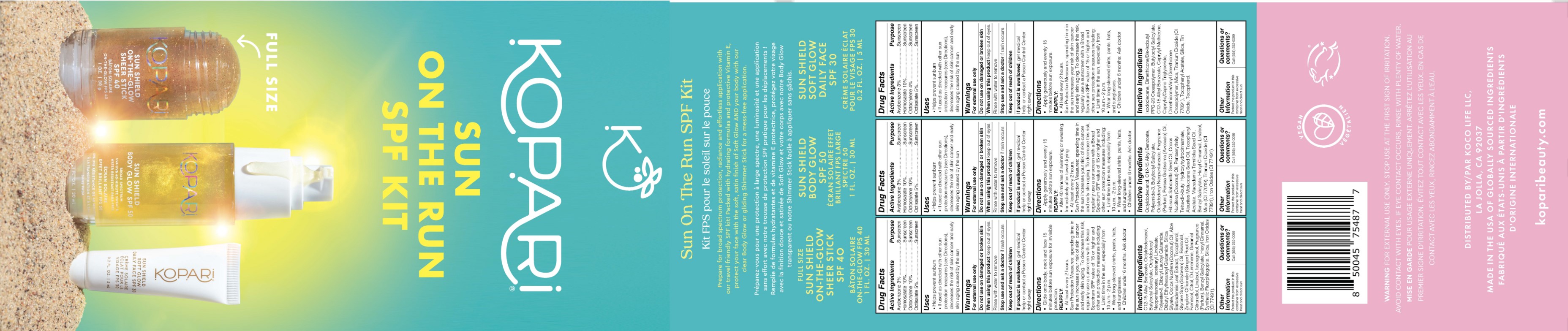 DRUG LABEL: Sun on the Run Kit
NDC: 84130-009 | Form: KIT | Route: TOPICAL
Manufacturer: Koco Life LLC
Category: otc | Type: HUMAN OTC DRUG LABEL
Date: 20240701

ACTIVE INGREDIENTS: HOMOSALATE 10 g/100 g; OCTISALATE 5 g/100 g; OCTOCRYLENE 10 g/100 g; AVOBENZONE 3 g/100 g; OCTISALATE 50 mg/1 mL; HOMOSALATE 100 mg/1 mL; OCTOCRYLENE 100 mg/1 mL; AVOBENZONE 30 mg/1 mL; OCTISALATE 50 mg/1 mL; HOMOSALATE 100 mg/1 mL; AVOBENZONE 30 mg/1 mL; OCTOCRYLENE 40 mg/1 mL
INACTIVE INGREDIENTS: SOYBEAN OIL; FARNESOL; CITRAL; .ALPHA.-HEXYLCINNAMALDEHYDE; BENZYL SALICYLATE; LINALOOL, (+)-; GINGER; COCONUT OIL; BUTYLOCTYL SALICYLATE; ALKYL (C12-15) BENZOATE; OCTYLDODECANOL; ISOSTEARYL LINOLEATE; DIBUTYL LAUROYL GLUTAMIDE; TOCOPHEROL; MAGNESIUM POTASSIUM ALUMINOSILICATE FLUORIDE; SILICON DIOXIDE; FERRIC OXIDE RED; SUNFLOWER OIL; ALOE VERA LEAF; OCTYLDODECYL NEOPENTANOATE; POLYESTER-8 (1400 MW, CYANODIPHENYLPROPENOYL CAPPED); DIBUTYL ETHYLHEXANOYL GLUTAMIDE; LEVOMENOL; MACADAMIA OIL; OCTYLDODECYL NEOPENTANOATE; COCONUT OIL; KUKUI NUT OIL; TITANIUM DIOXIDE; MICA; FERRIC OXIDE RED; LINALOOL, (+)-; PENTAERYTHRITOL TETRAKIS(3-(3,5-DI-TERT-BUTYL-4-HYDROXYPHENYL)PROPIONATE); BENZYL SALICYLATE; .ALPHA.-HEXYLCINNAMALDEHYDE; AVOCADO OIL; HIBISCUS SABDARIFFA SEED OIL; .ALPHA.-TOCOPHEROL ACETATE; ALKYL (C12-15) BENZOATE; OCTYLDODECANOL; BUTYLOCTYL SALICYLATE; POLYAMIDE-3 (12000 MW); .ALPHA.-TOCOPHEROL ACETATE; TOCOPHEROL; ALKYL (C12-15) BENZOATE; TITANIUM DIOXIDE; MEDIUM-CHAIN TRIGLYCERIDES; ISODODECANE; BUTYLOCTYL SALICYLATE; DIMETHICONE/VINYL DIMETHICONE CROSSPOLYMER (HARD PARTICLE); MICA; STANNOUS OXIDE; CAPRYLYL TRISILOXANE; SILICON DIOXIDE; DIMETHICONE/BIS-ISOBUTYL PPG-20 CROSSPOLYMER

Sun on the Run Kit

84130-001-10 Sun Shield Body Glow SPF50 DX

Active ingredients

Avobenzone 3%

Homosalate 10%

Octocrylene 10%

Octisalate 5%

Purpose

Avobenzone 3% .........................Sunscreen

Homosalate 10%.........................Sunscreen

Octocrylene 10% ........................Sunscreen

Octisalate 5% .............................Sunscreen

Uses

• Helps prevent sunburn

• If used as directed with other sunprotection measures (see Directions),decreases the risk of skin cancer and earlyskin aging caused by the sun

Warnings

For external use only

Do not use on damaged or broken skin

When using this product keep out of eyes
Rinse with water to remove

Stop use and ask a doctor if rash occurs

Keep out of reach of children
If product is swallowed, get medical help or contact a Poison Control Center right away

Directions

• Apply generously & evenly 15 minutesbefore sun exposure.

REAPPLY: After 40 minutes of swimming or sweating. • Immediately after towel drying.• At least every 2 hours

Sun Protection Measures: Spending time in the sun increases your risk of skin cancer and early skin aging. To decrease this risk, regularly use a sunscreen with a Broad Spectrum SPF value of 15 or higher and other sun protection measures including: • Limit time in the sun, especially from 10 a.m.- 2 p.m. • Wear long-sleeved shirts, pants, hats, and sunglasses • Children under 6 months: Ask a doctor

Inactive ingredients

Octyldodecanol, C12-15 Alkyl Benzoate, Polyamide-3, Butyloctyl Salicylate, Octyldodecyl Neopentanoate, Fragrance (Parfum), Persea Gratissima (Avocado) Oil, Hibiscus Sabdariffa Seed Oil, Cocos Nucifera (Coconut) Oil, Pentaerythrityl Tetra-di-t-butyl Hydroxyhydrocinnamate, Aleurites Moluccana Seed Oil, Tocopheryl Acetate, Macadamia Ternifolia Seed Oil, Benzyl Salicylate, Hexyl Cinnamal, Linalool, Mica (CI 77019), Titanium Dioxide (CI 77891), Iron Oxides (CI 77491).

Other information

Protect the product in this container from excessive heat and direct sun

Questions or comments?

Call (858) 252-0099

84130-004-10 Sun Shield On-the-Glow Sheer Stick SPF40

Active ingredients

Avobenzone 3%, Homosalate 10%, Octocrylene 10%, Octisalate 5%

Purpose

Avobenzone 3%, Homosalate 10%, Octocrylene 10%, Octisalate 5%.................................................................Sunscreen

Uses

• Helps prevent sunburn • If used as directed with other sun protection measures (see Directions), decreases the risk of skin cancer & early skin aging caused by the sun

Warnings

For external use only

Do not use on damaged or broken skin

When using this product keep out of eyes. Rinse with water to remove.

Stop use and ask a doctor if rash occurs

Keep out of reach of children. If product is swallowed, get medical help or contact a Poison Control Center right away.

Directions

• Glide onto body, neck and face 15 minutesbefore sun exposure for invisible protection.

Reapply: After 40 minutes of swimming or sweating. •Immediately after towel drying. • At least every 2 hours

Sun Protection Measures: Spending time in the sun increases your risk of skin cancer & early skin aging. To decrease this risk, regularly use a sunscreen with a Broad Spectrum SPF value of 15 or higher & other sun protection measures including:• Limit time in the sun, especially from 10 a.m. - 2 p.m• Wear long-sleeved shirts, pants, hats and sunglasses• Children under 6 months: Ask a doctor

Inactive ingredients

C12-15 Alkyl Benzoate, Octyldodecanol, Butyloctyl Salicylate, Octyldodecyl Neopentanoate, Isostearyl Linoleate, Dibutyl Lauroyl Glutamide, Polyester-8, Dibutyl Ethylhexanoyl Glutamide, Silica Silylate, Zingiber Officinale (Ginger) Root Extract, Tocopherol, Cocos Nucifera (Coconut) Oil, Helianthus Annuus (Sunflower) Seed Oil, Aloe Barbadensis Leaf Extract, Glycine Soja (Soybean) Oil, Bisabolol, Fragrance (Parfum), Synthetic Fluorphlogopite, Silica, Hexyl Cinnamal, Benzyl Salicylate, Linalool, Farnesol, Citral, CI 77491 (Iron Oxides).

Other information

Protect the product in this container from excessive heat and direct sun

Questions/Comments

Call (858) 252-0099

84130-006-21 Sun Shield Soft Glow Daily Face SPF30 DX

Active ingredients

Avobenzone 3%

Homosalate 10%

Octisalate 5%

Octocrylene 4%

Purpose

Avobenzone 3%.....................Sunscreen

Homosalate 10%...................Sunscreen

Octisalate 5%.......................Sunscreen

Octocrylene 4%.....................Sunscreen

Uses

• Helps prevent sunburn

• If used as directed with other sunprotection measures (see Directions),decreases the risk of skin cancer andearly skin aging caused by the sun

Warnings

• For external use only

• Do not use on damaged or broken skin

• Do not use on damaged or broken skin

• When using this product keep out of eyes• Rinse with water to remove

• Stop use and ask a doctor if rash occurs

• Keep out of reach of children

• If product is swallowed, get medicalhelp or contact a Poison ControlCenter right away

Directions

For Sunscreen use:

• Apply generously and evenly15 minutes before sun exposure.

REAPPLY:

• At least every 2 hours

Sun Protection Measures: spending time in the sun increases your risk of skin cancer and early skin aging. To decrease this risk, regularly use a sunscreen with a Broad Spectrum SPF value of 15 or higher and other sun protection measures including:• Limit time in the sun, especially from 10 a.m.- 2 p.m.• Wear long-sleeved shirts, pants, hats,and sunglasses.• Children under 6 months: Ask doctor

Inactive ingredients

Isododecane, Dimethicone/Bis-lsobutyl PPG-20 Crosspolymer, Butyloctyl Salicylate, C12-15 Alkyl Benzoate, Caprylyl Methicone, Caprylic/Capric Triglyceride, Dimethicone/Vinyl Dimethicone Crosspolymer, Mica, Titanium Dioxide (Cl 77891), Tocopheryl Acetate, Silica, Tin Oxide, Tocopherol.

Other information

Protect the product in this container from excessive heat and direct sun

Questions or comments?

Call (858) 252-0099